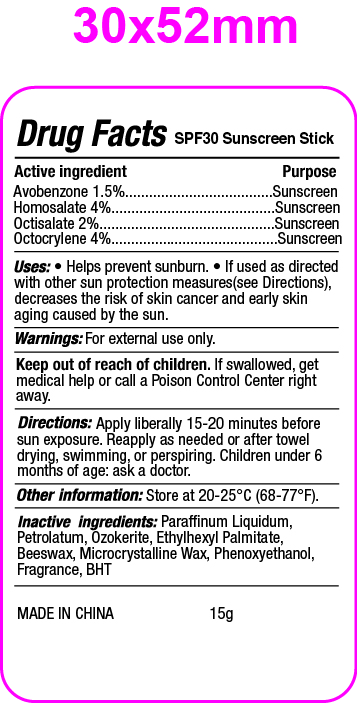 DRUG LABEL: Sunscreen stick
NDC: 82953-006 | Form: STICK
Manufacturer: Cosmuses Cosmetics (Ningbo) Co., Ltd.
Category: otc | Type: HUMAN OTC DRUG LABEL
Date: 20241204

ACTIVE INGREDIENTS: OCTOCRYLENE 4 g/100 g; AVOBENZONE 1.5 g/100 g; HOMOSALATE 4 g/100 g; OCTISALATE 2 g/100 g
INACTIVE INGREDIENTS: MINERAL OIL; CERESIN; BUTYLATED HYDROXYTOLUENE; ETHYLHEXYL PALMITATE; MICROCRYSTALLINE WAX; PHENOXYETHANOL; PETROLATUM; YELLOW WAX

SPF30 sunblock stick

Active ingredient

Avobenzone 1.5%

Homosalate 4%

Octisalate 2%

Octocrylene 4%

Purpose

Sunscreen

Uses

- Helps prevent sunburn
- If used as directed with other sun protection measures(see Directions), decreases the risk of skin cancer and early skin aging caused by the sun.

Warnings

For external use only.

Keep out of reach of children. If swallowed, get medical help or call a Poison Control Center right away.

Directions

Apply liberally 15-20 minutes before sun exposure. Reapply as needed or after towel drying, swimming or perspiring. Children under 6 months of age: ask a doctor.

Other information:

Store at 20-25oC (68-77oF).

Inactive ingredients:

Paraffinum liquidum, Petrolatum, Ozokerite, Ethylhexyl Palmitate, beeswax, Microcrystalline Wax, Phenoxyethanol, Fragrance, BHT